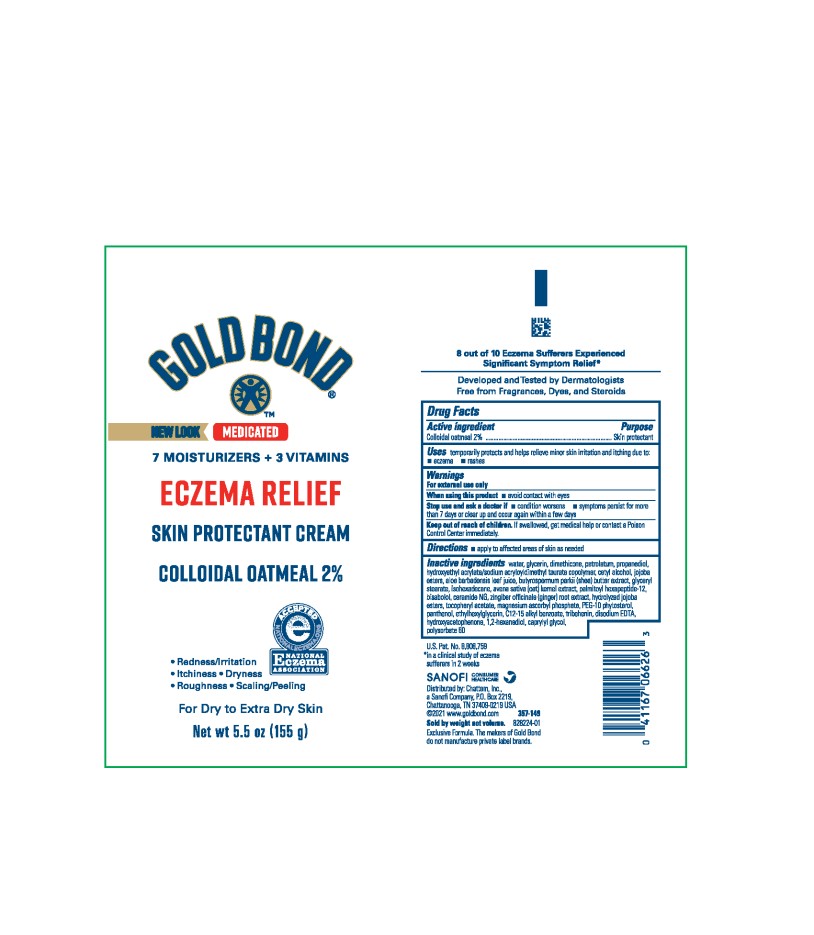 DRUG LABEL: Gold Bond Medicated eczema relief
NDC: 41167-0567 | Form: CREAM
Manufacturer: Chattem, Inc.
Category: otc | Type: HUMAN OTC DRUG LABEL
Date: 20260114

ACTIVE INGREDIENTS: OATMEAL 20 mg/1 g
INACTIVE INGREDIENTS: WATER; GLYCERIN; DIMETHICONE; PETROLATUM; PROPANEDIOL; HYDROXYETHYL ACRYLATE/SODIUM ACRYLOYLDIMETHYL TAURATE COPOLYMER (45000 MPA.S AT 1%); CETYL ALCOHOL; JOJOBA OIL, RANDOMIZED; ALOE VERA LEAF; SHEA BUTTER; GLYCERYL MONOSTEARATE; ISOHEXADECANE; OAT; PALMITOYL HEXAPEPTIDE-12; LEVOMENOL; CERAMIDE NG; GINGER; HYDROLYZED JOJOBA ESTERS (ACID FORM); ALPHA-TOCOPHEROL ACETATE; MAGNESIUM ASCORBYL PHOSPHATE; PANTHENOL; ETHYLHEXYLGLYCERIN; ALKYL (C12-15) BENZOATE; TRIBEHENIN; EDETATE DISODIUM ANHYDROUS; HYDROXYACETOPHENONE; 1,2-HEXANEDIOL; CAPRYLYL GLYCOL; POLYSORBATE 60

Gold Bond Eczema Relief Medicated Skin Protectant

Drug Facts

Active ingredient

Colloidal oatmeal 2%

Purpose

Skin protectant

Uses

temporarily protects and helps relieve minor skin irritation and itching due to:

- eczema
- rashes

Warnings

For external use only

When using this product

- avoid contact with eyes

Stop use and ask a doctor if

- condition worsens
- symptoms persist for more than 7 days or clear up and occur again within a few days

Keep out of reach of children.

If swallowed, get medical help or contact a Poison Control Center immediately.

Directions

- apply to affected areas of skin as needed

Inactive ingredients

water, glycerin, dimethicone, petrolatum, propanediol, hydroxyethyl acrylate/sodium acryloyldimethyl taurate copolymer, cetyl alcohol, jojoba esters, aloe barbadensis leaf juice, butyrospermum parkii (shea) butter extract, glyceryl stearate, isohexadecane, avena sativa (oat) kernel extract, palmitoyl hexapeptide-12, bisabolol, ceramide NG, zingiber officinale (ginger) root extract, hydrolyzed jojoba esters, tocopheryl acetate, magnesium ascorbyl phosphate, PEG-10 phytosterol, panthenol, ethylhexylglycerin, C12-15 alkyl benzoate, tribehenin, disodium EDTA, hydroxyacetophenone, 1,2-hexanediol, caprylyl glycol, polysorbate 60

PRINCIPAL DISPLAY PANEL

7 moisturizers & 3 vitamins
GOLD BOND®
2 % colloidal oatmeal
ECZEMA RELIEF
Skin Protectant Cream
Net wt 5.5 oz (155 g)